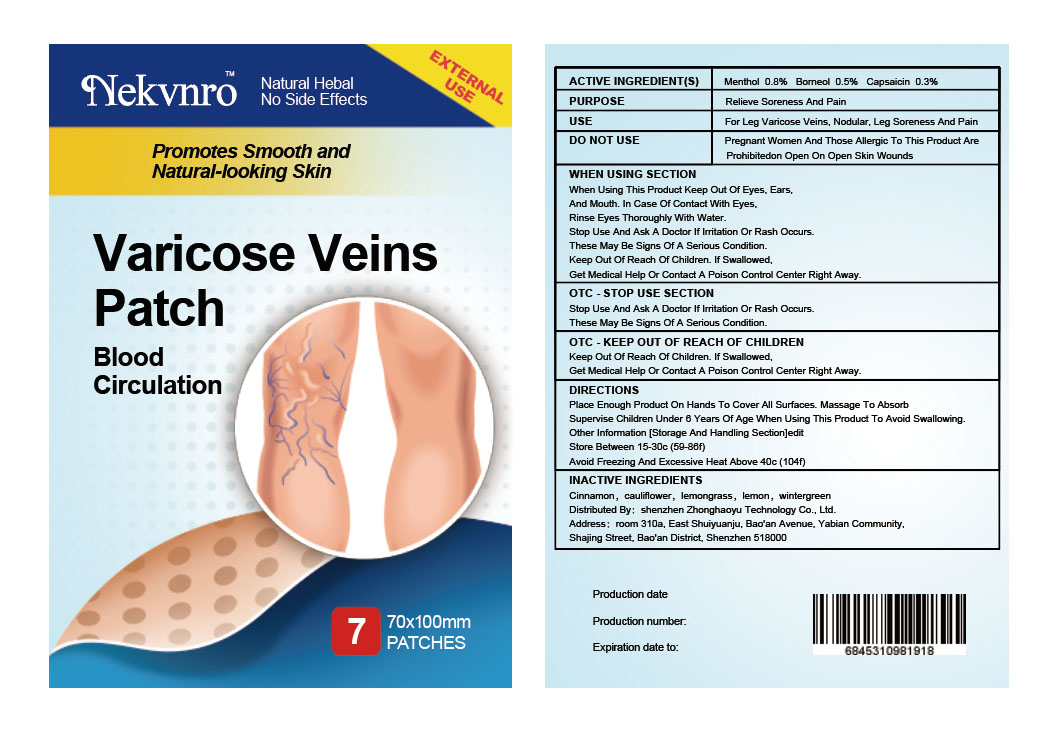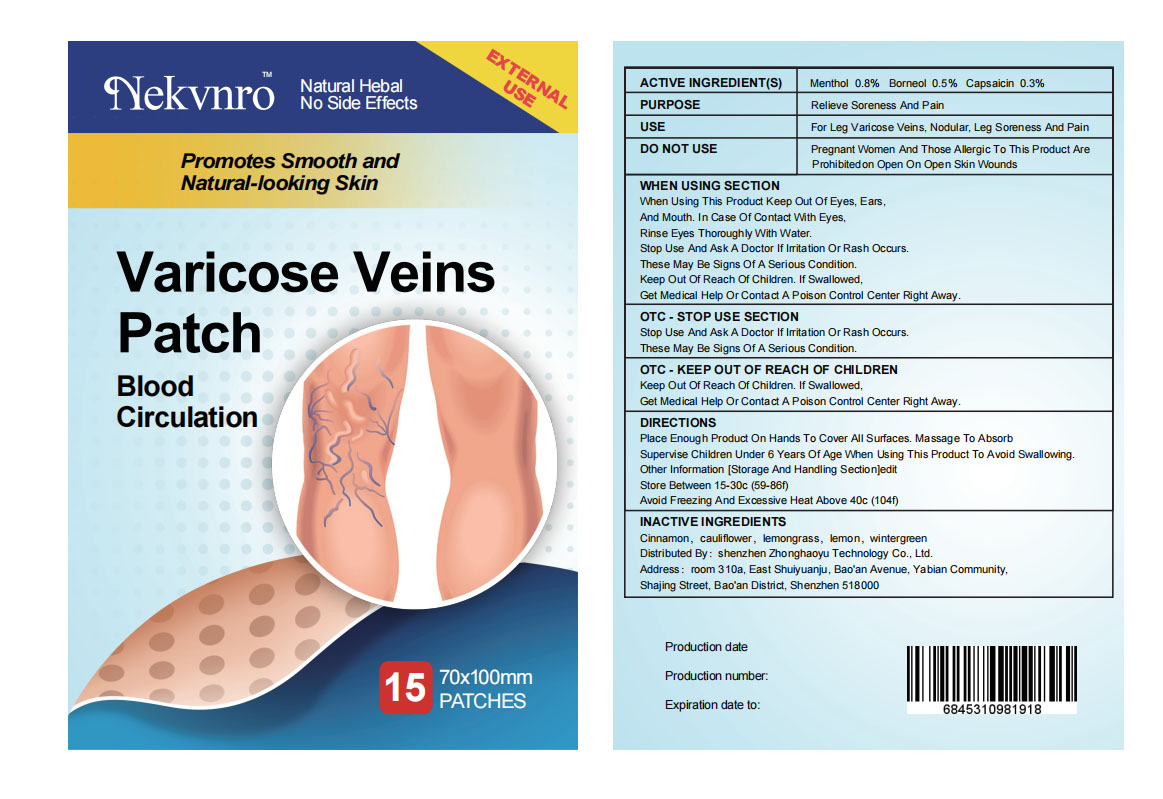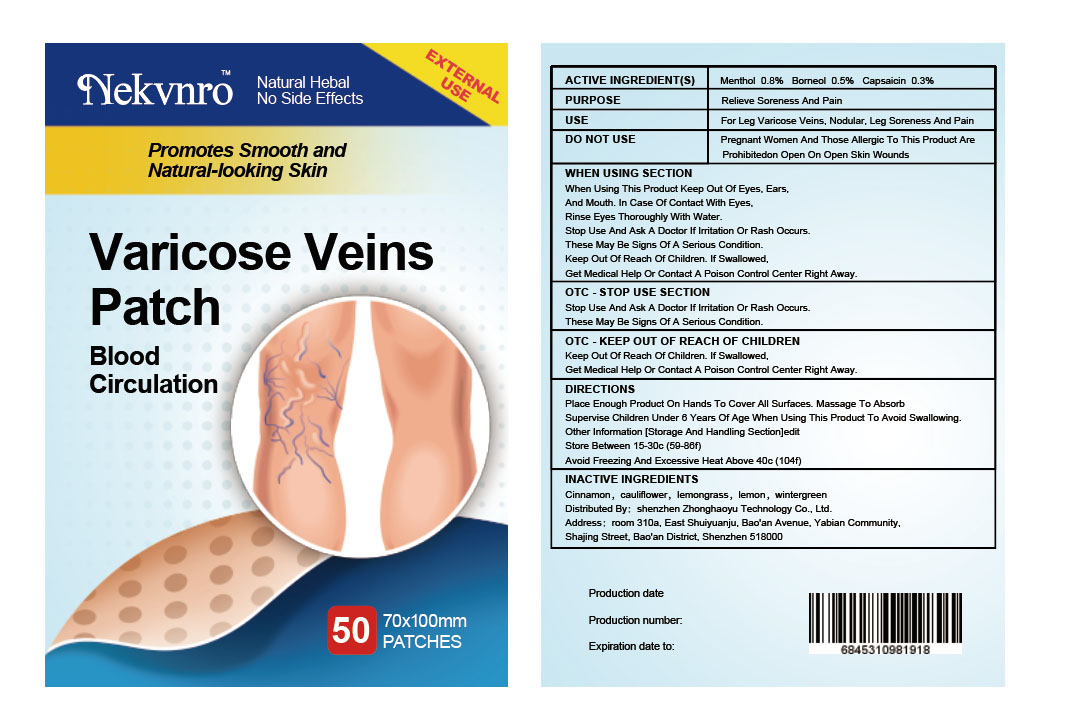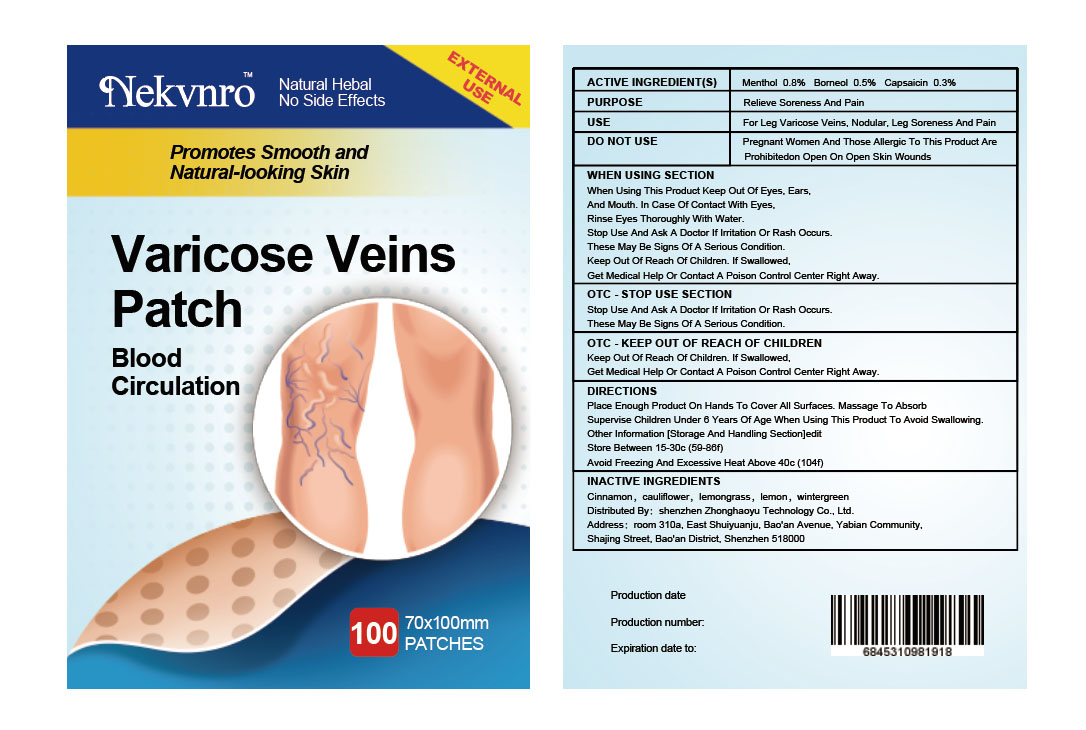 DRUG LABEL: Nekvnro Varicose Veins Patch
NDC: 82877-002 | Form: PATCH
Manufacturer: Shenzhen Boceda New Technology Co., Ltd.
Category: homeopathic | Type: HUMAN OTC DRUG LABEL
Date: 20220905

ACTIVE INGREDIENTS: MENTHOL 0.8 g/100 1; CAPSAICIN 0.3 g/100 1; BORNEOL 0.5 g/100 1
INACTIVE INGREDIENTS: CINNAMON; CAULIFLOWER; CYMBOPOGON CITRATUS LEAF; LEMON; METHYL SALICYLATE

82877-002
Nekvnro Varicose Veins Patch

ACTIVE INGREDIENT(S)

Menthol 0.8%

Borneol 0.5%

Capsaicin 0.3%

PURPOSE

Relieve Soreness And Pain

USE

For Leg Varicose Veins, Nodular, Leg Soreness And Pain

WARNINGS

n/a

DO NOT USE

Pregnant Women And Those Allergic To This Product Are
Prohibitedon Open On Open Skin Wounds

WHEN USING SECTION

When Using This Product Keep Out Of Eyes, Ears,
And Mouth. In Case Of Contact With Eyes,
Rinse Eyes Thoroughly With Water.
Stop Use And Ask A Doctor If Irritation Or Rash Occurs.
These May Be Signs Of A Serious Condition.
Keep Out Of Reach Of Children. If Swallowed,
Get Medical Help Or Contact A Poison Control Center Right Away.

OTC - STOP USE SECTION

Stop Use And Ask A Doctor If Irritation Or Rash Occurs.
These May Be Signs Of A Serious Condition.

OTC - KEEP OUT OF REACH OF CHILDREN

Keep Out Of Reach Of Children. If Swallowed,
Get Medical Help Or Contact A Poison Control Center Right Away.

DIRECTIONS

Place Enough Product On Hands To Cover All Surfaces. Massage To Absorb
Supervise Children Under 6 Years Of Age When Using This Product To Avoid Swallowing.
Other Information [Storage And Handling Section]edit
Store Between 15-30c (59-86f)
Avoid Freezing And Excessive Heat Above 40c (104f)

STORAGE AND HANDLING

Store Between 15-30c (59-86f)
Avoid Freezing And Excessive Heat Above 40c (104f)

INACTIVE INGREDIENTS

Cinnamon，cauliflower，lemongrass，lemon，wintergreen